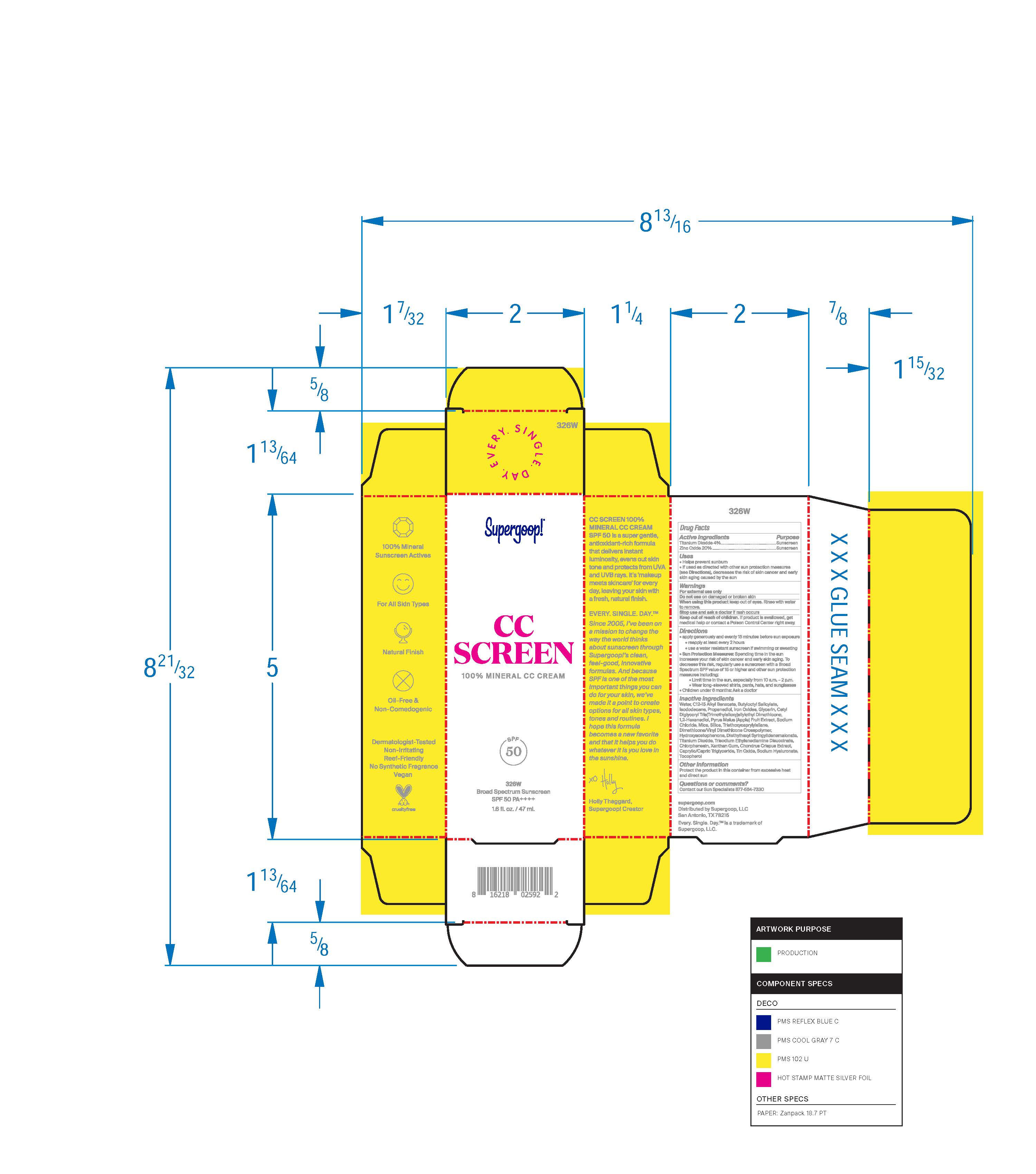 DRUG LABEL: CC Screen 100% Mineral CC Cream Broad Spectrum SPF 50 326W
NDC: 75936-232 | Form: CREAM
Manufacturer: Supergoop, LLC
Category: otc | Type: HUMAN OTC DRUG LABEL
Date: 20241206

ACTIVE INGREDIENTS: ZINC OXIDE 20 g/100 mL; TITANIUM DIOXIDE 4 g/100 mL
INACTIVE INGREDIENTS: HYDROXYACETOPHENONE; FERROSOFERRIC OXIDE; BUTYLOCTYL SALICYLATE; ISODODECANE; GLYCERIN; MEDIUM-CHAIN TRIGLYCERIDES; STANNIC OXIDE; HYALURONATE SODIUM; TOCOPHEROL; FERRIC OXIDE YELLOW; CHONDRUS CRISPUS CARRAGEENAN; SODIUM CHLORIDE; TRIETHOXYCAPRYLYLSILANE; DIMETHICONE/VINYL DIMETHICONE CROSSPOLYMER (SOFT PARTICLE); MICA; FERRIC OXIDE RED; PROPANEDIOL; 1,2-HEXANEDIOL; APPLE; SILICON DIOXIDE; TRISODIUM ETHYLENEDIAMINE DISUCCINATE; CHLORPHENESIN; XANTHAN GUM; WATER; ALKYL (C12-15) BENZOATE; DIETHYLHEXYL SYRINGYLIDENEMALONATE

CC Screen 100% Mineral CC Cream Broad Spectrum SPF 50 326W

Active Ingredients Purpose

Titanium Dioxide 4% Sunscreen

Zinc Oxide 20% Sunscreen

Uses

- Helps Prevent Sunburn
- If used as directed with other sun protection measures (see Directions), decreases the risk of skin cancer and early skin aging caused by the sun.

Keep out of reach of children. If product is swallowed, get medical help or contact a poison Control Center right away

Stop use and ask a doctor if rash occurs.

Warnings

- For external use only
- Do not use on damaged or broken skin
- When using this product keep out of eyes. Rinse with water to remove

Directions

Apply generously and evenly 15 minutes before sun exposure
Use a water-resistant sunscreen if swimming or sweating
Reapply at least every 2 hours.
Sun Protection Measures Spending time in the sun increases your risk of
skin cancer and early skin aging. To decrease this risk, regularly use a
sunscreen with a Broad-Spectrum SPF value of 15 or higher and other sun
protection measures including:

• limit your time in the sun, especially from 10
a.m. – 2 p.m. • wear long-sleeved shirts, pants, hats, and sunglasses

• Children under 6 months of age: ask a doctor.

Inactive Ingredients

Water, C12-15 Alkyl Benzonate, Butyoctyl Salicylate, Isododecane, Propanediol, Iron Oxides, Glycerin, Cetyl Diglyceryl Tris(Trimethylsiloxy) siloxysilylethyl Dimethicone, 1,2-Hexanediol, Pyrus Malus (Apple) Fruit Extract, Sodium Chloride, Mica, Silica, Triethoxycaprylylsilane, Dimethicone/Vinyl Dimethicone Crosspolymer, Hydroxyacetophenone, Diethylhexyl Syringylidenemalonate, Titanium Dioxide, Trisodium Ethylenediamine Disuccinate, Chlorphenesin, Xanthan Gum, Chondrus Crispus Extract, Caprylic/Capric Triglyceride, Tin Oxide, Sodium Hyaluronate, Tocopherol

PACKAGE LABEL

CC screen 100% Mineral CC Cream 326W

SPF 50

Broad Spectrum Sunscreen SPF 50 PA+++

1.6 fl. oz. / 47 ml.